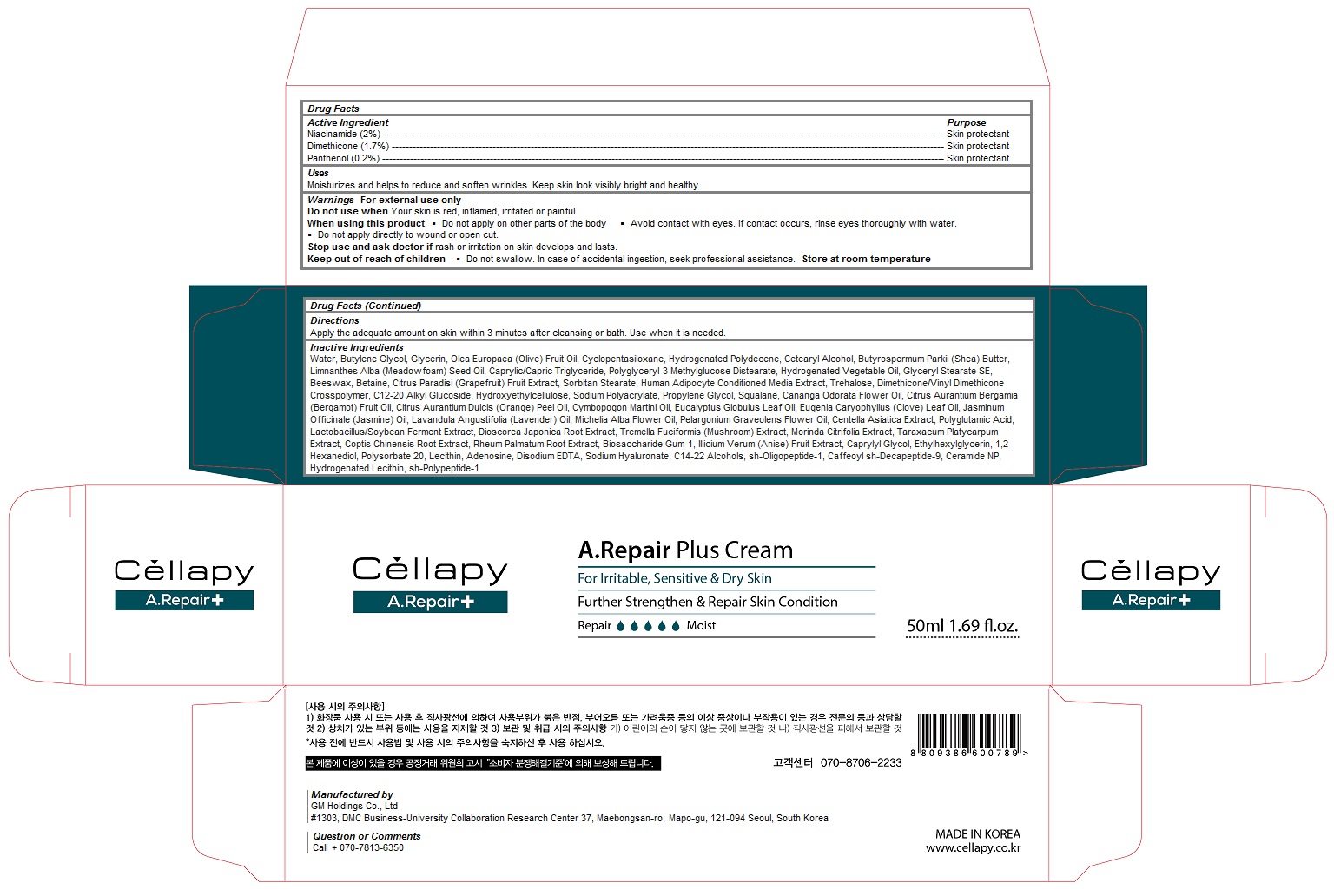 DRUG LABEL: Cellapy A.Repair Plus
NDC: 69278-108 | Form: CREAM
Manufacturer: Gm Holdings Co., Ltd
Category: otc | Type: HUMAN OTC DRUG LABEL
Date: 20161228

ACTIVE INGREDIENTS: Niacinamide 1 g/50 mL; Dimethicone 0.85 g/50 mL; Panthenol 0.1 g/50 mL
INACTIVE INGREDIENTS: WATER; Butylene Glycol; OLIVE OIL; CYCLOMETHICONE 5; HYDROGENATED POLYDECENE (550 MW); CETOSTEARYL ALCOHOL; SHEA BUTTER; MEADOWFOAM SEED OIL; MEDIUM-CHAIN TRIGLYCERIDES; CORN OIL; GLYCERYL STEARATE SE; YELLOW WAX; Betaine; GRAPEFRUIT; SORBITAN MONOSTEARATE; Trehalose; DIMETHICONE/VINYL DIMETHICONE CROSSPOLYMER (HARD PARTICLE); C12-20 ALKYL GLUCOSIDE; HYDROXYETHYL CELLULOSE (100 MPA.S AT 2%); SODIUM POLYACRYLATE (2500000 MW); PROPYLENE GLYCOL; Squalane; CANANGA OIL; BERGAMOT OIL; ORANGE OIL; PALMAROSA OIL; EUCALYPTUS OIL; CLOVE LEAF OIL; JASMINUM OFFICINALE FLOWER; LAVENDER OIL; MAGNOLIA X ALBA FLOWER OIL; PELARGONIUM GRAVEOLENS FLOWER OIL; CENTELLA ASIATICA; DIOSCOREA JAPONICA TUBER; MORINDA CITRIFOLIA LEAF; COPTIS CHINENSIS ROOT; RHEUM PALMATUM ROOT; BIOSACCHARIDE GUM-1; STAR ANISE FRUIT; CAPRYLYL GLYCOL; ETHYLHEXYLGLYCERIN; 1,2-HEXANEDIOL; POLYSORBATE 20; EGG PHOSPHOLIPIDS; Adenosine; HYALURONATE SODIUM; C14-22 ALCOHOLS; NEPIDERMIN; CERAMIDE NP; HYDROGENATED SOYBEAN LECITHIN; BASIC FIBROBLAST GROWTH FACTOR (HUMAN)

Cellapy A.Repair Plus Cream

Active Ingredients

Niacinamide (2%)

Dimethicone (1.7%)

Panthenol (0.2%)

Purpose

Skin protectant

Directions

Apply the adequate amount on skin within 3 minutes after cleansing or bath. Use when it is needed.

Uses

Moisturizes and helps to reduce and soften wrinkles. Keep skin look visibly bright and healthy.

Warnings

For external use only
Do not use when Your skin is red, inflamed, irritated or painful
When using this product
 Do not apply on other parts of the body
 Avoid contact with eyes. If contact occurs, rinse eyes thoroughly with water.
 Do not apply directly to wound or open cut.
Stop use and ask doctor if rash or irritation on skin develops and lasts.

Keep out of reach of children

 Do not swallow. In case of accidental ingestion, seek professional assistance.

Inactive Ingredients

Water, Butylene Glycol, Glycerin, Olea Europaea (Olive) Fruit Oil, Cyclopentasiloxane, Hydrogenated Polydecene, Cetearyl Alcohol, Butyrospermum Parkii (Shea) Butter, Limnanthes Alba (Meadowfoam) Seed Oil, Caprylic/Capric Triglyceride, Polyglyceryl-3 Methylglucose Distearate, Hydrogenated Vegetable Oil, Glyceryl Stearate SE, Beeswax, Betaine, Citrus Paradisi (Grapefruit) Fruit Extract, Sorbitan Stearate, Human Adipocyte Conditioned Media Extract, Trehalose, Dimethicone/Vinyl Dimethicone Crosspolymer, C12-20 Alkyl Glucoside, Hydroxyethylcellulose, Sodium Polyacrylate, Propylene Glycol, Squalane, Cananga Odorata Flower Oil, Citrus Aurantium Bergamia (Bergamot) Fruit Oil, Citrus Aurantium Dulcis (Orange) Peel Oil, Cymbopogon Martini Oil, Eucalyptus Globulus Leaf Oil, Eugenia Caryophyllus (Clove) Leaf Oil, Jasminum Officinale (Jasmine) Oil, Lavandula Angustifolia (Lavender) Oil, Michelia Alba Flower Oil, Pelargonium Graveolens Flower Oil, Centella Asiatica Extract, Polyglutamic Acid, Lactobacillus/Soybean Ferment Extract, Dioscorea Japonica Root Extract, Tremella Fuciformis (Mushroom) Extract, Morinda Citrifolia Extract, Taraxacum Platycarpum Extract, Coptis Chinensis Root Extract, Rheum Palmatum Root Extract, Biosaccharide Gum-1, Illicium Verum (Anise) Fruit Extract, Caprylyl Glycol, Ethylhexylglycerin, 1,2-Hexanediol, Polysorbate 20, Lecithin, Adenosine, Disodium EDTA, Sodium Hyaluronate, C14-22 Alcohols, sh-Oligopeptide-1, Caffeoyl sh-Decapeptide-9, Ceramide NP, Hydrogenated Lecithin, sh-Polypeptide-1